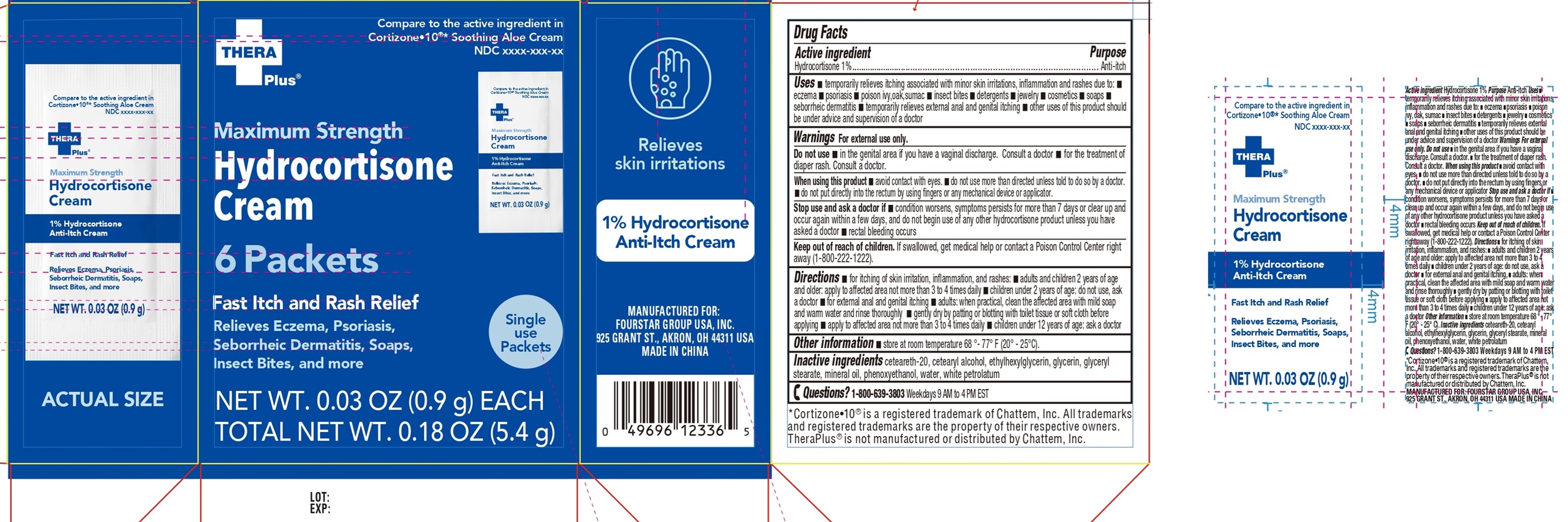 DRUG LABEL: Thera Plus Maximum Strength Hydrocortisone
NDC: 80684-197 | Form: CREAM
Manufacturer: Fourstar Group USA, Inc
Category: otc | Type: HUMAN OTC DRUG LABEL
Date: 20251202

ACTIVE INGREDIENTS: HYDROCORTISONE 10 mg/1 g
INACTIVE INGREDIENTS: CETEARETH-20; CETEARYL ALCOHOL; ETHYLHEXYLGLYCERIN; GLYCERIN; GLYCERYL STEARATE; MINERAL OIL; PHENOXYETHANOL; WATER; WHITE PETROLATUM

Thera Plus Maximum Strength Hydrocortisone Cream

Active ingredient

Hydrocortisone 1%

Purpose

Anti-itch

Uses

• temporarily relieves itching associated with minor skin irritations, inflammation and rashes due to: • eczema • psoriasis • poison ivy,oak, sumac • insect bites • detergents • jewelry • cosmetics • soaps • seborrheic dermatitis • temporarily relieves external anal and gential itching • other uses of this product should be under advice and supervision of a doctor

Warnings

For external use only.

Do not use

• in the genital area if you have a vaginal discharge. Consult a doctor • for the treatment of diaper rash. Consult a doctor.

When using this product

• avoid contact with eyes. • do not use more than directed unless told to do so by a doctor. • do not put directly into the rectum by using fingers or any mechanical device or applicator.

Stop use and ask a doctor if

• condition worsens, symptoms persists for more than 7 days or clear up and occur again within a few days, and do not begin use of any other hydrocortisone product unless you have asked a doctor • rectal bleeding occurs

Keep out of reach of children.

If swallowed, get medical help or contact a Poison Control Center right away (1-800-222-1222).

Directions

• for itching of skin irritation, inflammation, and rashes: • adults and children 2 years of age and older: apply to affected area not more than 3 to 4 times daily • children under 2 years of age: do not use, ask a doctor • for external anal and genital itching • adults: when practical, clean the affected area with mild soap and warm water and rinse thoroughly • gently dry by patting or blotting with toilet tissue or soft cloth before applying • apply to affected area not more than 3 to 4 times daily • children under 12 years of age: ask a doctor

Other information

• store at room temperature 68 °- 77° F (20°-25°C).

Inactive ingredients

ceteareth-20, cetearyl alcohol, ethylhexylglycerin, glycerin, glyceryl stearate, mineral oil, phenoxyethanol, water, white petrolatum

Questions?

1-800-639-3803Weekdays 9 AM to 4 PM EST